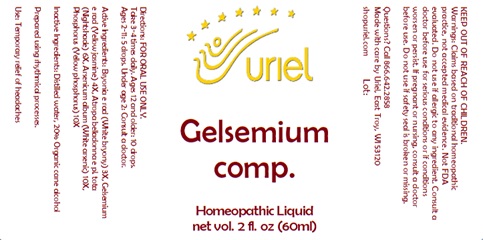 DRUG LABEL: Gelsemium comp.
NDC: 48951-5140 | Form: LIQUID
Manufacturer: Uriel Pharmacy, Inc.
Category: homeopathic | Type: HUMAN OTC DRUG LABEL
Date: 20241023

ACTIVE INGREDIENTS: GELSEMIUM SEMPERVIRENS ROOT 4 [hp_X]/1 mL; BRYONIA ALBA ROOT 3 [hp_X]/1 mL; ATROPA BELLADONNA 6 [hp_X]/1 mL; ARSENIC TRIOXIDE 10 [hp_X]/1 mL; PHOSPHORUS 10 [hp_X]/1 mL
INACTIVE INGREDIENTS: ALCOHOL; WATER

Gelsemium comp.

INDICATIONS AND USAGE

Directions: FOR ORAL USE ONLY.

DOSAGE AND ADMINISTRATION

Take 3-4 times daily. Ages 12 and older: 10 drops.
Ages 2-11: 5 drops. Under age 2: Consult a doctor.

ACTIVE INGREDIENT

Active Ingredients: Bryonia e rad (White bryony) 3X, Gelsemium e rad (Yellow jasmine) 4X, Atropa belladonna e pl. tota (Nightshade) 6X, Arsenicum album (White arsenic) 10X, Phosphorus (Yellow phosphorus) 10X

Inactive Ingredients: Distilled water, 20% Organic cane alcohol

Prepared using rhythmical processes

PURPOSE

Use: Temporary relief of headaches

KEEP OUT OF REACH OF CHILDREN.

WARNINGS

Warnings: Claims based on traditional homeopathic practice, not accepted medical evidence. Not FDA evaluated. Do not use if allergic to any ingredient. Consult a doctor before use for serious conditions or if conditions worsen or persist. If pregnant or nursing, consult a doctor before use. Do not use if safety seal is broken or missing.

Questions? Call 866.642.2858
Made with care by Uriel, East Troy, WI 53120
shopuriel.com Lot: